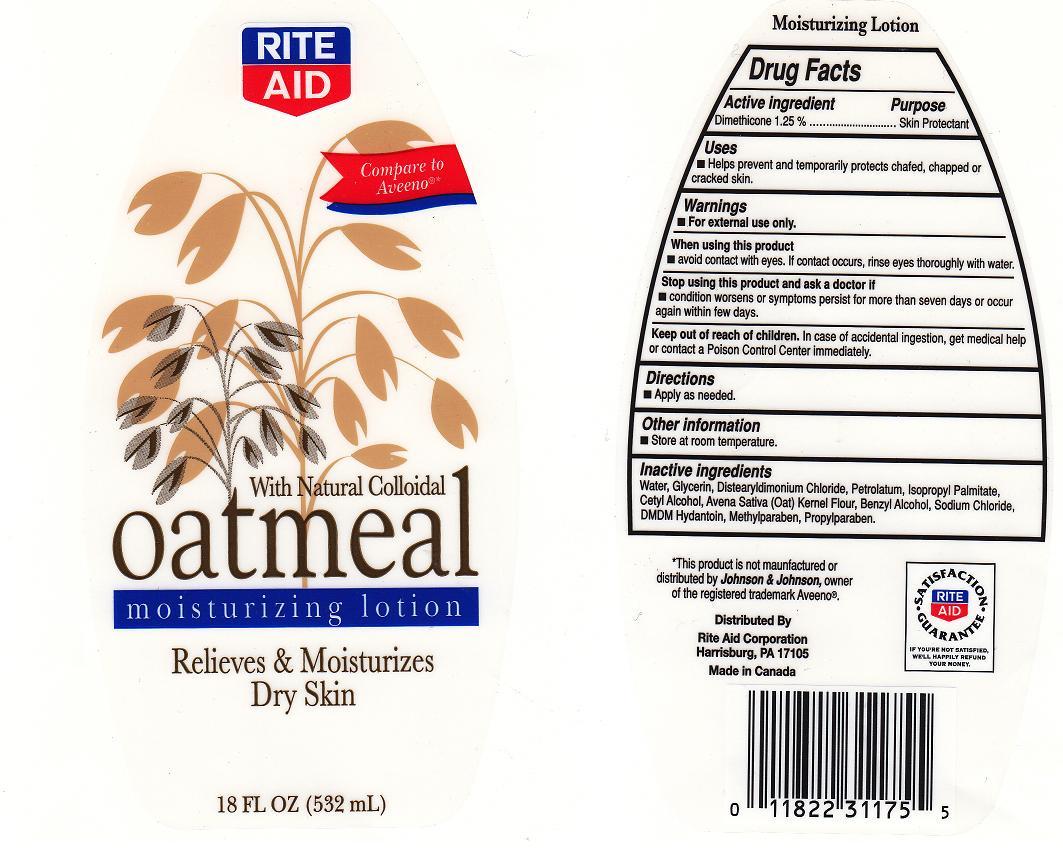 DRUG LABEL: DAILY MOISTURIZING 
NDC: 11822-3201 | Form: LOTION
Manufacturer: RITE AID CORPORATION
Category: otc | Type: HUMAN OTC DRUG LABEL
Date: 20100625

ACTIVE INGREDIENTS: DIMETHICONE 1.2500 mL/100 mL

BACK LABEL - DRUG FACTS BOX

ACTIVE INGREDIENT

DIMETHICONE 1.25% (SKIN PROTECTANT)

WARNING

FOR EXTERNAL USE ONLY.

WHEN USING

AVOID CONTACT WITH EYES, IF CONTACT OCCURS, RINSE EYE THROUGHLY WITH WATER.

STOP USING THIS PRODUCT AND ASK A DOCTOR IF

CONDITION WORSENS OR SYMPTOMS PERSIST FOR MORE THAN SEVEN DAYS OR OCCUR AGAIN WITHIN A FEW DAYS.

KEEP OUT OF REACH OF CHILDREN

IN CASE OF ACCIDENTAL INGESTION, GET MEDICAL HELP OR CONTACT A POISON CONTROL CENTER IMMEDIATELY.

USES AND DIRECTIONS

- USES: HELPS PREVENT AND TEMPORARILY PROTECTS CHAFED, CHAPPED OR CRACKED SKIN.

- DIRECTIONS: APPLY AS NEEDED.

FRONT AND BACK LABELS

- 18OZ FRONT AND BACK LABELS: ra18.jpg

OTHER INFORMATION

STORE AT ROOM TEMPERATURE.